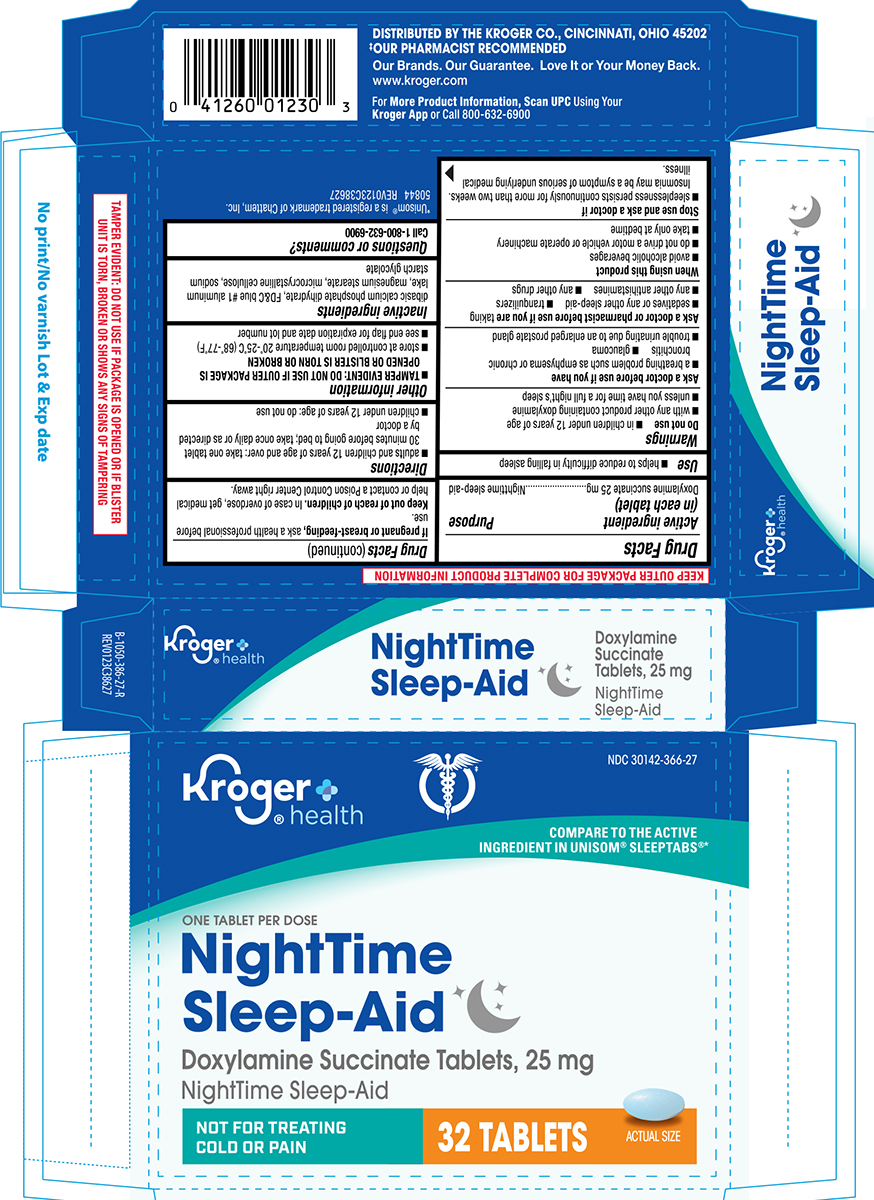 DRUG LABEL: Nighttime Sleep-Aid
NDC: 30142-366 | Form: TABLET
Manufacturer: Kroger Company
Category: otc | Type: HUMAN OTC DRUG LABEL
Date: 20250923

ACTIVE INGREDIENTS: DOXYLAMINE SUCCINATE 25 mg/1 1
INACTIVE INGREDIENTS: DIBASIC CALCIUM PHOSPHATE DIHYDRATE; FD&C BLUE NO. 1 ALUMINUM LAKE; MAGNESIUM STEARATE; MICROCRYSTALLINE CELLULOSE; SODIUM STARCH GLYCOLATE TYPE A POTATO

Kroger 44-386

Active ingredient (in each tablet)

Doxylamine succinate 25 mg

Purpose

Nighttime sleep-aid

Use

- helps to reduce difficulty in falling asleep

Warnings

Do not use

- in children under 12 years of age
- with any other product containing doxylamine
- unless you have time for a full night’s sleep

Ask a doctor before use if you have

- glaucoma
- a breathing problem such as emphysema or chronic bronchitis
- trouble urinating due to an enlarged prostate gland

Ask a doctor or pharmacist before use if you are

taking

- sedatives or any other sleep-aid
- tranquilizers
- any other antihistamines
- any other drugs

When using this product

- avoid alcoholic beverages
- do not drive a motor vehicle or operate machinery
- take only at bedtime

Stop use and ask a doctor if

- sleeplessness persists continuously for more than two weeks. Insomnia may be a symptom of serious underlying medical illness.

If pregnant or breast-feeding,

ask a health professional before use.

Keep out of reach of children.

In case of overdose, get medical help or contact a Poison Control Center right away.

Directions

- adults and children 12 years of age and over: take one tablet 30 minutes before going to bed; take once daily or as directed by a doctor
- children under 12 years of age: do not use

Other information

- TAMPER EVIDENT: DO NOT USE IF OUTER PACKAGE IS OPENED OR BLISTER IS TORN OR BROKEN
- store at controlled room temperature 20°-25°C (68°-77°F)
- see end flap for expiration date and lot number

Inactive ingredients

dibasic calcium phosphate dihydrate, FD&C blue #1 aluminum lake, magnesium stearate, microcrystalline cellulose, sodium starch glycolate

Questions or comments?

1-800-632-6900

Principal Display Panel

Kroger
®health

NDC 30142-366-27

COMPARE TO THE ACTIVE
INGREDIENT IN UNISOM® SLEEPTABS®*

ONE TABLET PER DOSE

NightTime
Sleep-Aid

Doxylamine Succinate Tablet, 25 mg
NightTime Sleep-Aid

NOT FOR TREATING
COLD OR PAIN

32 TABLETS

ACTUAL SIZE

TAMPER EVIDENT: DO NOT USE IF PACKAGE IS OPENED OR IF BLISTER
UNIT IS TORN, BROKEN OR SHOWS ANY SIGNS OF TAMPERING

*Unisom® is a registered trademark of Chattem, Inc.
50844 REV0123C38627

DISTRIBUTED BY THE KROGER CO., CINCINNATI, OHIO 45202
‡OUR PHARMACIST RECOMMENDED
Our Brands. Our Guarantee. Love It or Your Money Back.
www.kroger.com

For More Product Information, Scan UPC Using Your
Kroger App or Call 800-632-6900

Kroger 44-386